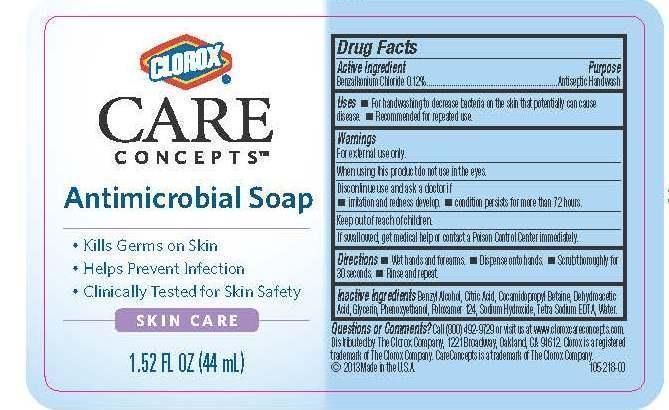 DRUG LABEL: Clorox Care Concepts Antimicrobial
NDC: 26509-0003 | Form: SOAP
Manufacturer: The Clorox Company
Category: otc | Type: HUMAN OTC DRUG LABEL
Date: 20141114

ACTIVE INGREDIENTS: BENZALKONIUM CHLORIDE .12 g/100 mL
INACTIVE INGREDIENTS: BENZYL ALCOHOL; CITRIC ACID MONOHYDRATE; COCAMIDOPROPYL BETAINE; DEHYDROACETIC ACID; GLYCERIN; PHENOXYETHANOL; POLOXAMER 124; SODIUM HYDROXIDE; EDETATE SODIUM; WATER

Drug Facts

Active ingredient

Benzalkonium chloride 0.12%

Purpose

Antiseptic handwash

Use

- For handwashing to decrease bacteria on skin that potentially can cause disease
- Recommended for repeated use

Warnings

For external use only.

When using this product, do not use in the eyes.

Discontinue use and ask a doctor if

- irritate and redness develop.
- condition persists for more than 72 hours.

Keep out of reach of children.

If swallowed, get medical help or contact a Poison Control Center immediately.

Directions

- Wet hands and forearms.
- Dispense onto hands.
- Scrub thoroughly for 30 seconds.
- Rinse and repeat.

Inactive ingredients

Benzyl Alcohol, Citric Acid, Cocamidopropyl Betaine, Dehydroacetic Acid, Glycerin, Phenoxyethanol, Poloxamer 124, Sodium Hydroxide, Tetra Sodium EDTA, Water

PACKAGE LABEL

Clorox Care Concepts

Antimicrobial Soap